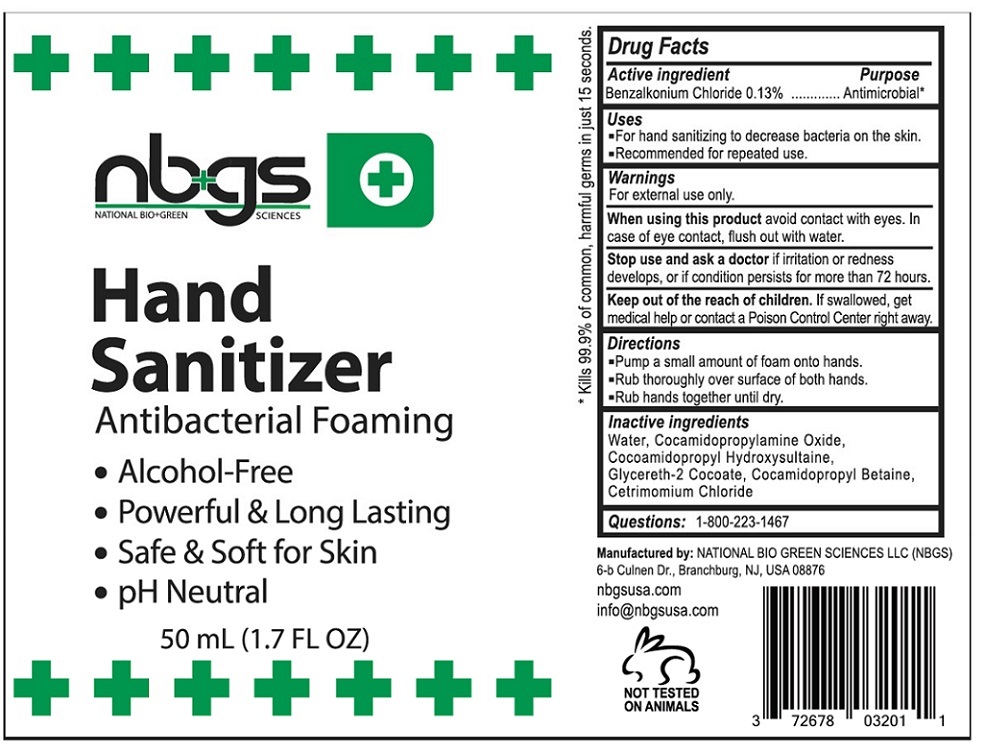 DRUG LABEL: NBGS Hand Sanitizer
NDC: 72678-032 | Form: SOLUTION
Manufacturer: National Bio Green Sciences Limited Liability Company
Category: otc | Type: HUMAN OTC DRUG LABEL
Date: 20200422

ACTIVE INGREDIENTS: BENZALKONIUM CHLORIDE 1.3 mg/1 mL
INACTIVE INGREDIENTS: WATER; COCAMIDOPROPYLAMINE OXIDE; COCAMIDOPROPYL HYDROXYSULTAINE; GLYCERETH-2 COCOATE; COCAMIDOPROPYL BETAINE; CETRIMONIUM CHLORIDE

NBGS Hand Sanitizer

Active ingredient

Benzalkonium chloride 0.13%

Purpose

Antimicrobial*

Uses

- For hand sanitizing to decrease bacteria on the skin.
- Recommended for repeated use.

Warnings

For external use only.

When using this product avoid contact with eyes. In case of eye contact, flush out with water.

Stop use and ask a doctor if irritation or redness develops, or if condition persists for more than 72 hours.

Keep out of reach of children. If swallowed, get medical help or contact a Poison Control Center right away.

Directions

- Pump a small amount of foam onto hands.
- Rub thoroughly over surface of both hands.
- Rub hands together until dry.

Inactive ingredients

Water, Cocamidopropylamine Oxide, Cocamidopropyl Hydroxysultaine, Glycereth-2 Cocoate, Cocamidopropyl Betaine, Cetrimonium Chloride.

Questions: 1-800-223-1467

Antibacterial Foaming

- Alcohol-Free
- Powerful & Long Lasting
- Safe & Soft for Skin
- pH Neutral

*Kills 99.9% of common, harmful germs in just 15 seconds.

Manufactured by: NATIONAL BIO GREEN SCIENCES LLC (NBGS)

6-b Culnen Dr., Branchburg, NJ, USA 08876

nbgsusa.com

info@nbgsusa.com

NOT TESTED ON ANIMALS